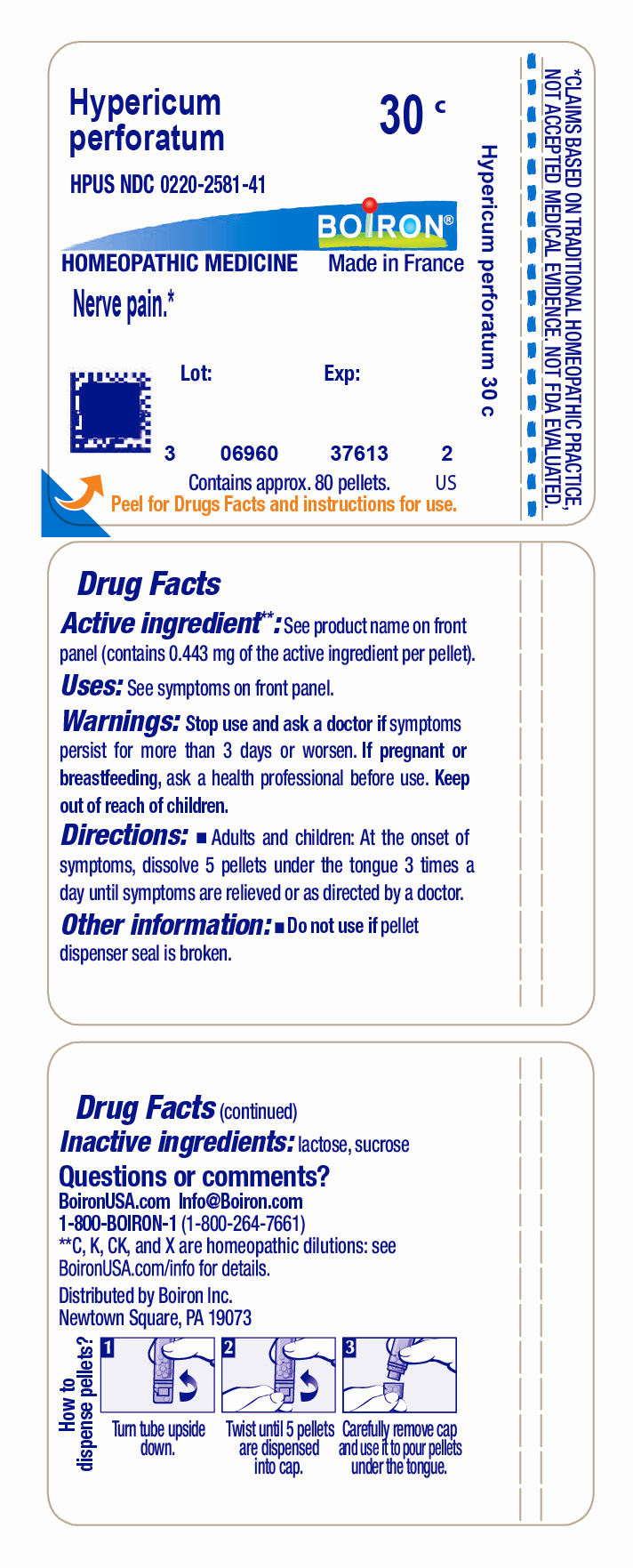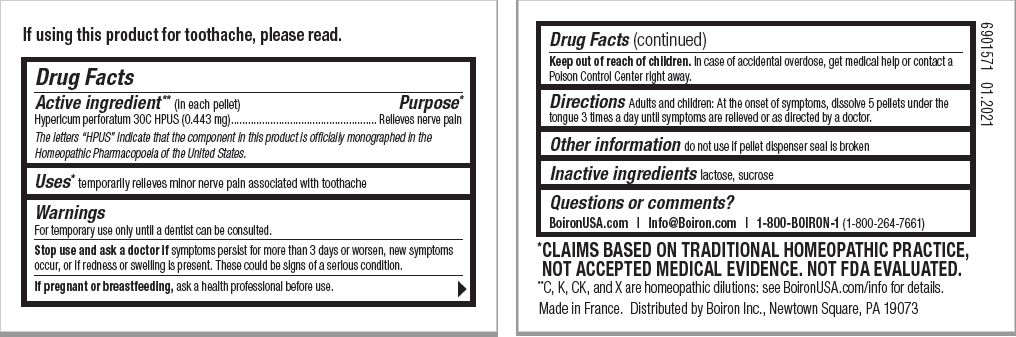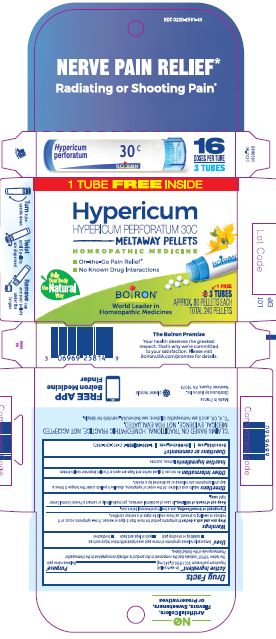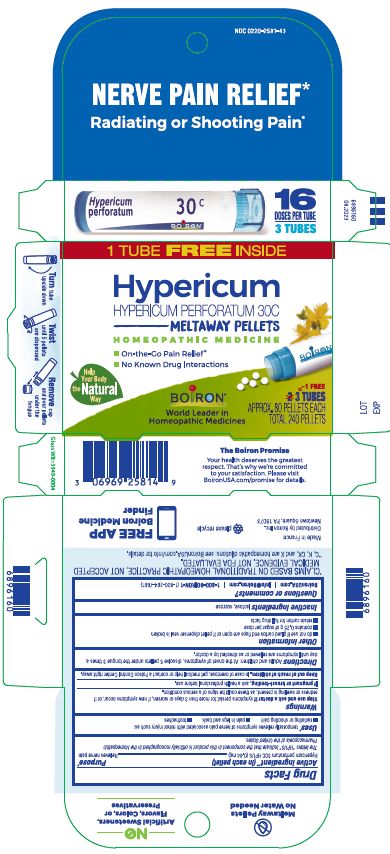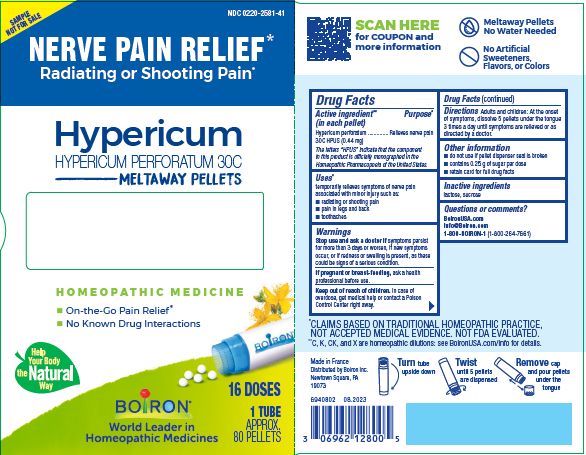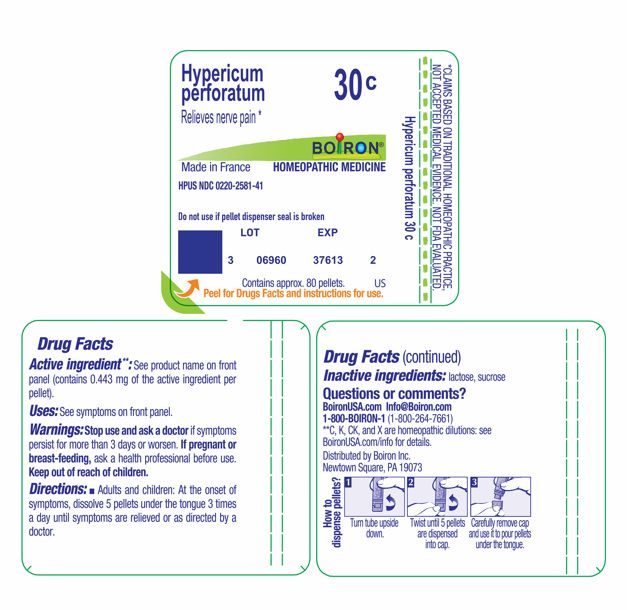 DRUG LABEL: Hypericum perforatum
NDC: 0220-2581 | Form: PELLET
Manufacturer: Boiron
Category: homeopathic | Type: HUMAN OTC DRUG LABEL
Date: 20251230

ACTIVE INGREDIENTS: HYPERICUM PERFORATUM 30 [hp_C]/30 [hp_C]
INACTIVE INGREDIENTS: LACTOSE, UNSPECIFIED FORM; SUCROSE

Hypericum perforatum 30C

Active ingredient**(in each pellet)

Hypericum perforatum 30C HPUS (0.44 mg)

The letters "HPUS" indicate that the components in this product are officially monographed in the Homeopathic Pharmacopoeia of the United States.

Purpose*

Relieves nerve pain

Uses*

temporarily relieves symptoms of nerve pain associated with minor injury such as:

- radiating or shooting pain
- pain in legs and back
- toothaches

WARNINGS

Tube - (If using this product for toothache) For temporary use only until a dentist can be consulted.

STOP USE

Box - Stop use and ask a doctor if symptoms persist for more than 3 days or worsen, if new symptoms occur, or if redenss or swelling is present, as these could be signs of serious condition.

Tube - (If using this product for toothache) Stop use and ask a doctor if symptoms persist for more than 3 days or worsen, if new symptoms occur, or if redenss or swelling is present, as these could be signs of serious condition.

PREGNANCY OR BREAST FEEDING

If pregnant or breast-feeding, ask a health professional before use.

KEEP OUT OF REACH OF CHILDREN

Box - Keep out of reach of children. In case of overdose, get medical help or contact a Poison Control Center right away.

Tube - (If using this product for toothache) Keep out of reach of children. In case of accidental overdose, get medical help or contact a Poison Control Center right away.

DOSAGE AND ADMINISTRATION

Adults and children: At the onset of symptoms, dissolve 5 pellets under the tongue 3 times a day until symptoms are relieved or as directed by a doctor.

INACTIVE INGREDIENT

lactose, sucrose

QUESTIONS

1-800-BOIRON-1 (1-800-264-7661),

BoironUSA.com Info@boiron.com
Distributed by Boiron, Inc. Newtown Square, PA 19073

Tube - Do not use if pellet dispenser seal is broken.
Contains approx 80 pellets.
How to dispense pellets? Turn tube upside down. Twist until 5 pellets are dispensed into cap. Carefully remove the cap and use it to pour pellets under the tongue.
*CLAIMS BASED ON TRADITIONAL HOMEOPATHIC PRACTICE NOT ACCEPTED MEDICAL EVIDENCE. NOT FDA EVALUATED.
*C,K,CK, and X are homeopathic dilutions: see BoironUSA.com/info for details.

Box - Do not use if glued carton end flaps are open or if pellet dispenser seal is broken.

3 Tubes approx 80 pellets 16 Doses per tube Total 240 pellets

1 Tube approx 80 pellets 16 Doses 80 pellets

How to dispense pellets? Turn tube upside down. Twist until 5 pellets are dispensed. Remove cap and pour pellets under the tongue.

Never Pain Relief*

Radiating or Shooting Pain*

*CLAIMS BASED ON TRADITIONAL HOMEOPATHIC PRACTICE NOT ACCEPTED MEDICAL EVIDENCE. NOT FDA EVALUATED.
*C,K,CK, and X are homeopathic dilutions: see BoironUSA.com/info for details.